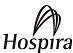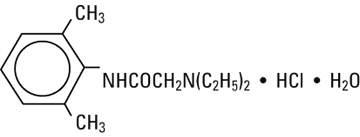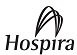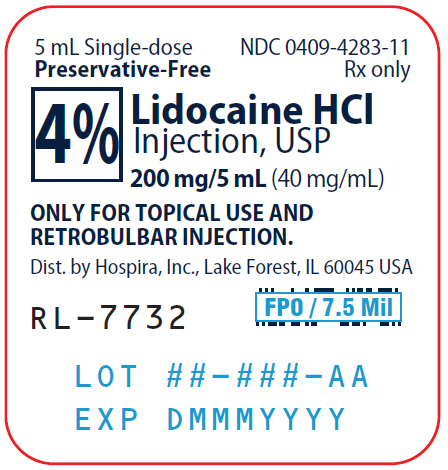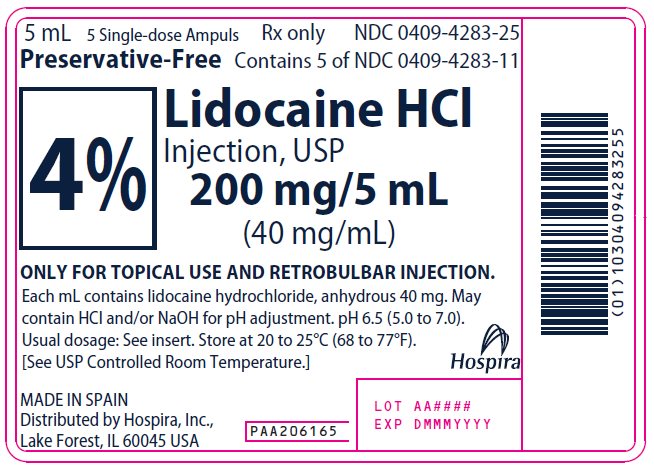 DRUG LABEL: Lidocaine Hydrochloride
NDC: 0409-4283 | Form: INJECTION, SOLUTION
Manufacturer: Hospira, Inc.
Category: prescription | Type: HUMAN PRESCRIPTION DRUG LABEL
Date: 20241128

ACTIVE INGREDIENTS: LIDOCAINE HYDROCHLORIDE 40 mg/1 mL
INACTIVE INGREDIENTS: WATER; SODIUM HYDROXIDE; HYDROCHLORIC ACID

4% Lidocaine Hydrochloride
Injection, USP (40 mg/mL)
AQUEOUS SOLUTION FOR TOPICAL USE
AND RETROBULBAR INJECTION

Rx only

DESCRIPTION

4% Lidocaine Hydrochloride Injection, USP is a sterile, nonpyrogenic solution containing lidocaine hydrochloride, anhydrous 40 mg/mL in water for injection. May contain sodium hydroxide and/or hydrochloric acid for pH adjustment. pH 6.5 (5.0 to 7.0).

Lidocaine has cardiac antiarrhythmic properties and is a local anesthetic of the amide type.

Lidocaine Hydrochloride, USP is chemically designated 2-(diethylamino)-2′,6′-acetoxylidide monohydrochloride monohydrate, a white powder freely soluble in water. It has the following structural formula:

CLINICAL PHARMACOLOGY

Mechanism of action: Lidocaine stabilizes the neuronal membrane by inhibiting the ionic fluxes required for the initiation and conduction of impulses, thereby effecting local anesthetic action.

Onset and duration of anesthesia: The onset of action is rapid. For retrobulbar injection, 4 mL of 4% Lidocaine Hydrochloride Injection, USP provides an average duration of action of 1 to 1.5 hours. This duration may be extended for ophthalmic surgery by the addition of epinephrine, the usual recommended dilution being 1:50,000 to 1:100,000.

Hemodynamics: Excessive blood levels may cause changes in cardiac output, total peripheral resistance, and mean arterial pressure. These changes may be attributable to a direct depressant effect of the local anesthetic agent on various components of the cardiovascular system. The net effect is normally a modest hypotension when the recommended dosages are not exceeded.

Pharmacokinetics and metabolism: Information derived from other formulations, concentrations and usages reveals that lidocaine is completely absorbed following parenteral administration, its rate of absorption depending, for example, upon such factors such as the site of administration and the presence or absence of a vasoconstrictor agent. Lidocaine may be absorbed following topical administration to mucous membranes, its rate and extent of absorption depending upon concentration and total dose administered, the specific site of application and duration of exposure. In general, the rate of absorption of local anesthetic agents following topical application occurs most rapidly after intratracheal administration. Lidocaine is also well absorbed from the gastrointestinal tract, but intact drug appears in the circulation because of biotransformation by the liver.

Lidocaine is metabolized rapidly by the liver, and metabolites and unchanged drug are excreted by the kidneys. Biotransformation includes oxidative N-dealkylation, ring hydroxylation, cleavage of the amide linkage, and conjugation. N-dealkylation, a major pathway of biotransformation, yields the metabolites monoethylglycinexylidide and glycinexylidide. The pharmacological/toxicological actions of these metabolites are similar to, but less potent than, those of lidocaine. Approximately 90% of lidocaine administered is excreted in the form of various metabolites, and less than 10% is excreted unchanged. The primary metabolite in urine is a conjugate of 4-hydroxy-2,6-dimethylaniline.

Studies have shown that peak blood levels of lidocaine may occur as early as 5 and as late as 30 minutes after endotracheal administration of a 4% lidocaine HCl injection.

The plasma binding of lidocaine is dependent on drug concentration, and the fraction bound decreases with increasing concentration. At concentrations of 1 to 4 mcg of free base per mL, 60 to 80 percent of lidocaine is protein bound. Binding is also dependent on the plasma concentration of the alpha-1-acid glycoprotein.

Lidocaine crosses the blood-brain and placental barriers, presumably by passive diffusion.

Studies of lidocaine metabolism following intravenous bolus injections have shown that the elimination half-life of this agent is typically 1.5 to 2.0 hours. Because of the rapid rate at which lidocaine is metabolized, any condition that affects liver function may alter lidocaine kinetics. The half-life may be prolonged two-fold or more in patients with liver dysfunction. Renal dysfunction does not affect lidocaine kinetics but may increase the accumulation of metabolites.

Factors such as acidosis and the use of central nervous system stimulants and depressants affect the central nervous system levels of lidocaine required to produce overt systemic effects. Objective adverse manifestations become increasingly apparent with increasing venous plasma levels above 6.0 mcg free base per mL. In the rhesus monkey arterial blood levels of 18–21 mcg/mL have been shown to be threshold for convulsive activity.

INDICATIONS AND USAGE

4% Lidocaine Hydrochloride Injection, USP is indicated for the production of topical anesthesia of the mucous membranes of the respiratory tract or the genito-urinary tract. It may be injected trans-tracheally to anesthetize the larynx and trachea, and it may be administered by retrobulbar injection to provide anesthesia for ophthalmic surgery.

CONTRAINDICATIONS

Lidocaine is contraindicated in patients with a known history of hypersensitivity to local anesthetics of the amide type.

WARNINGS

4% LIDOCAINE HYDROCHLORIDE INJECTION, USP SHOULD BE EMPLOYED ONLY BY CLINICIANS WHO ARE WELL VERSED IN DIAGNOSIS AND MANAGEMENT OF DOSE-RELATED TOXICITY AND OTHER ACUTE EMERGENCIES THAT MIGHT ARISE AND THEN ONLY AFTER ENSURING THE IMMEDIATE AVAILABILITY OF OXYGEN, OTHER RESUSCITATIVE DRUGS, CARDIOPULMONARY EQUIPMENT, AND THE PERSONNEL NEEDED FOR PROPER MANAGEMENT OF TOXIC REACTIONS AND RELATED EMERGENCIES (see also ADVERSE REACTIONS and PRECAUTIONS). DELAY IN PROPER MANAGEMENT OF DOSE-RELATED TOXICITY, UNDERVENTILATION FROM ANY CAUSE AND/OR ALTERED SENSITIVITY MAY LEAD TO THE DEVELOPMENT OF ACIDOSIS, CARDIAC ARREST AND, POSSIBLY, DEATH.

Methemoglobinemia

Cases of methemoglobinemia have been reported in association with local anesthetic use. Although all patients are at risk for methemoglobinemia, patients with glucose-6-phosphate dehydrogenase deficiency, congenital or idiopathic methemoglobinemia, cardiac or pulmonary compromise, infants under 6 months of age, and concurrent exposure to oxidizing agents or their metabolites are more susceptible to developing clinical manifestations of the condition. If local anesthetics must be used in these patients, close monitoring for symptoms and signs of methemoglobinemia is recommended.

Signs of methemoglobinemia may occur immediately or may be delayed some hours after exposure, and are characterized by a cyanotic skin discoloration and/or abnormal coloration of the blood. Methemoglobin levels may continue to rise; therefore, immediate treatment is required to avert more serious central nervous system and cardiovascular adverse effects, including seizures, coma, arrhythmias, and death. Discontinue lidocaine hydrochloride and any other oxidizing agents. Depending on the severity of the signs and symptoms, patients may respond to supportive care, i.e., oxygen therapy, hydration. A more severe clinical presentation may require treatment with methylene blue, exchange transfusion, or hyperbaric oxygen.

Intra-articular infusions of local anesthetics following arthroscopic and other surgical procedures is an unapproved use, and there have been post-marketing reports of chondrolysis in patients receiving such infusions. The majority of reported cases of chondrolysis have involved the shoulder joint; cases of gleno-humeral chondrolysis have been described in pediatric and adult patients following intra-articular infusions of local anesthetics with and without epinephrine for periods of 48 to 72 hours. There is insufficient information to determine whether shorter infusion periods are not associated with these findings. The time of onset of symptoms, such as joint pain, stiffness and loss of motion can be variable, but may begin as early as the 2nd month after surgery. Currently, there is no effective treatment for chondrolysis; patients who experienced chondrolysis have required additional diagnostic and therapeutic procedures and some required arthroplasty or shoulder replacement.

To avoid intravascular injection, aspiration should be performed before the local anesthetic solution is injected. The needle must be repositioned until no return of blood can be elicited by aspiration. Note, however, that the absence of blood in the syringe does not guarantee that intravascular injection has been avoided.

4% Lidocaine Hydrochloride Injection, USP should be used with extreme caution if there is sepsis or severely traumatized mucosa in the area of application, since under such conditions there is the potential for rapid systemic absorption.

PRECAUTIONS

General: The safety and effectiveness of lidocaine depend on proper dosage, correct technique, adequate precautions, and readiness for emergencies. Resuscitative equipment, oxygen and other resuscitative drugs should be available for immediate use (see WARNINGS and ADVERSE REACTIONS). The lowest dosage that results in effective anesthesia should be used to avoid high plasma levels and serious adverse effects. Repeated doses of lidocaine may cause significant increases in blood levels with each repeated dose, because of slow accumulation of the drug or its metabolites. Tolerance to elevated blood levels varies with the status of the patient. Debilitated, elderly patients, acutely ill patients, and children should be given reduced doses commensurate with their age and physical status. Lidocaine should also be used with caution in patients with severe shock or heart block.

Local anesthetic solutions containing a vasoconstrictor should be used cautiously and in carefully circumscribed quantities in areas of the body supplied by end arteries or having otherwise compromised blood supply. Patients with peripheral vascular disease and those with hypertensive vascular disease may exhibit exaggerated vasoconstrictor response. Ischemic injury or necrosis may result. Preparations containing a vasoconstrictor should be used with caution in patients during or following the administration of potent general anesthetic agents, since cardiac arrhythmias may occur under such conditions.

Careful and constant monitoring of cardiovascular and respiratory (adequacy of ventilation) vital signs and the patient's state of consciousness should be accomplished after each local anesthetic injection. It should be kept in mind at such times that restlessness, anxiety, tinnitus, dizziness, blurred vision, tremors, depression or drowsiness may be early warning signs of central nervous system toxicity.

Since amide-type local anesthetics are metabolized by the liver, lidocaine should be used with caution in patients with hepatic disease.

Patients with severe hepatic disease, because of their inability to metabolize local anesthetic normally, are at a greater risk of developing toxic plasma concentrations. Lidocaine should also be used with caution in patients with impaired cardiovascular function since they may be less able to compensate for functional changes associated with the prolongation of A-V conduction produced by these drugs.

Use in Ophthalmic Surgery: When local anesthetic solutions are employed for retrobulbar block, lack of corneal sensation should not be relied upon to determine whether or not the patient is ready for surgery since corneal sensation usually precedes clinically acceptable external ocular muscle akinesia.

Many drugs used during the conduct of anesthesia are considered potential triggering agents for familial malignant hyperthermia. Since it is not known whether amide-type local anesthetics may trigger this reaction and since the need for supplemental general anesthesia cannot be predicted in advance, it is suggested that a standard protocol for management should be available. Early unexplained signs of tachycardia, tachypnea, labile blood pressure and metabolic acidosis may precede temperature elevation. Successful outcome is dependent on early diagnosis, prompt discontinuance of the suspect triggering agent(s) and institution of treatment, including oxygen therapy, indicated supportive measures and dantrolene (consult dantrolene sodium intravenous package insert before using).

Lidocaine should be used with caution in persons with known drug sensitivities. Patients allergic to para-aminobenzoic acid derivatives (procaine, tetracaine, benzocaine, etc.) have not shown cross sensitivity to lidocaine.

Use in the Head and Neck Area: Small doses of local anesthetics injected into the head and neck area, including retrobulbar, dental and stellate ganglion blocks, may produce adverse reactions similar to systemic toxicity seen with unintentional intravascular injections of larger doses. Confusion, convulsions, respiratory depression and/or respiratory arrest, and cardiovascular stimulation or depression have been reported. These reactions may be due to intra-arterial injection of the local anesthetic with retrograde flow to the cerebral circulation. Patients receiving these blocks should have their circulation and respiration monitored and be constantly observed. Resuscitative equipment and personnel for treating adverse reactions should be immediately available. Dosage recommendations should not be exceeded (see DOSAGE AND ADMINISTRATION).

Information for Patients: When topical anesthetics are used in the mouth, the patient should be aware that the production of topical anesthesia may impair swallowing and thus enhance the danger of aspiration. For this reason, food should not be ingested for 60 minutes following use of local anesthetic preparations in the mouth or throat area. This is particularly important in children because of their frequency of eating.

Numbness of the tongue or buccal mucosa may enhance the danger of unintentional biting trauma. Food and chewing gums should not be taken while the mouth or throat area is anesthetized.

Inform patients that use of local anesthetics may cause methemoglobinemia, a serious condition that must be treated promptly. Advise patients or caregivers to seek immediate medical attention if they or someone in their care experience the following signs or symptoms: pale, gray, or blue colored skin (cyanosis); headache; rapid heart rate; shortness of breath; lightheadedness; or fatigue.

Clinically significant drug interactions: The administration of local anesthetic solutions containing epinephrine or nor-epinephrine to patients receiving monoamine oxidase inhibitors, tricyclic antidepressants or phenothiazines may produce severe, prolonged hypotension or hypertension. Concurrent use of these agents should generally be avoided. In situations when concurrent therapy is necessary, careful patient monitoring is essential.

Drug/Laboratory test interactions: The intramuscular injection of lidocaine may result in an increase in creatine phosphokinase levels. Thus, the use of this enzyme determination, without isoenzyme separation, as a diagnostic test for the presence of acute myocardiac infarction may be compromised by the intramuscular injection of lidocaine.

Patients who are administered local anesthetics are at increased risk of developing methemoglobinemia when concurrently exposed to the following drugs, which could include other local anesthetics:

Examples of Drugs Associated with Methemoglobinemia:

Class | Examples
Nitrates/Nitrites | nitric oxide, nitroglycerin, nitroprusside, nitrous oxide
Local anesthetics | articaine, benzocaine, bupivacaine, lidocaine, mepivacaine, prilocaine, procaine, ropivacaine, tetracaine
Antineoplastic agents | cyclophosphamide, flutamide, hydroxyurea, ifosfamide, rasburicase
Antibiotics | dapsone, nitrofurantoin, para-aminosalicylic acid, sulfonamides
Antimalarials | chloroquine, primaquine
Anticonvulsants | phenobarbital, phenytoin, sodium valproate
Other drugs | acetaminophen, metoclopramide, quinine, sulfasalazine

Carcinogenesis, mutagenesis, impairment of fertility: Studies of lidocaine in animals to evaluate the carcinogenic and mutagenic potential or the effect on fertility have not been conducted.

Use in Pregnancy: Teratogenic Effects. Reproduction studies have been performed in rats at doses up to 6.6 times the human dose and have revealed no evidence of harm to the fetus caused by lidocaine. There are, however, no adequate and well-controlled studies in pregnant women. Animal reproduction studies are not always predictive of human response. General consideration should be given to this fact before administering lidocaine to women of childbearing potential, especially during early pregnancy when maximum organogenesis takes place.

Labor and delivery: Lidocaine is not contraindicated in labor and delivery. Should 4% Lidocaine Hydrochloride Injection, USP be used concomitantly with other products containing lidocaine, the total dose contributed by all formulations must be kept in mind.

Nursing mothers: It is not known whether this drug is excreted in human milk. Because many drugs are excreted in human milk, caution should be exercised when lidocaine is administered to a nursing woman.

Pediatric use: Dosages in children should be reduced, commensurate with age and body weight (see DOSAGE AND ADMINISTRATION).

ADVERSE REACTIONS

Adverse experiences following the administration of lidocaine are similar in nature to those observed with other amide local anesthetic agents. These adverse experiences are, in general, dose-related and may result from high plasma levels caused by excessive dosage, rapid absorption or inadvertent intravascular injection, or may result from a hypersensitivity, idiosyncrasy or diminished tolerance on the part of the patient. Serious adverse experiences are generally systemic in nature. The following types are those most commonly reported:

Central nervous system: Central nervous system manifestations are excitatory and/or depressant and may be characterized by light-headedness, nervousness, apprehension, euphoria, confusion, dizziness, drowsiness, tinnitus, blurred or double vision, vomiting, sensations of heat, cold or numbness, twitching, tremors, convulsions, unconsciousness, respiratory depression and arrest. The excitatory manifestations may be very brief or may not occur at all, in which case the first manifestation of toxicity may be drowsiness merging into unconsciousness and respiratory arrest.

Drowsiness following the administration of lidocaine is usually an early sign of a high blood level of the drug and may occur as a consequence of rapid absorption.

Cardiovascular system: Cardiovascular manifestations are usually depressant and are characterized by bradycardia, hypotension, and cardiovascular collapse, which may lead to cardiac arrest.

Allergic: Allergic reactions are characterized by cutaneous lesions, urticaria, edema or anaphylactoid reactions. Allergic reactions as a result of sensitivity to lidocaine are extremely rare and, if they occur, should be managed by conventional means. The detection of sensitivity by skin testing is of doubtful value.

Neurologic: The incidences of adverse reactions associated with the use of local anesthetics may be related to the total dose of local anesthetic administered and are also dependent upon the particular drug used, the route of administration and the physical status of the patient.

OVERDOSAGE

Acute emergencies from local anesthetics are generally related to high plasma levels encountered during therapeutic use of local anesthetics or to unintended subarachnoid injection of local anesthetic solution (see ADVERSE REACTIONS, WARNINGS and PRECAUTIONS).

Management of local anesthetic emergencies: The first consideration is prevention, best accomplished by careful and constant monitoring of cardiovascular and respiratory vital signs and the patient's state of consciousness after each local anesthetic injection. At the first sign of change, oxygen should be administered.

The first step in the management of convulsions consists of immediate attention to the maintenance of a patent airway and assisted or controlled ventilation with oxygen and a delivery system capable of permitting immediate positive airway pressure by mask. Immediately after the institution of these ventilatory measures, the adequacy of the circulation should be evaluated, keeping in mind that drugs used to treat convulsions sometimes depress the circulation when administered intravenously. Should convulsions persist despite adequate respiratory support, and if the status of the circulation permits, small increments of an ultra-short acting barbiturate (such as thiopental or thiamylal) or a benzodiazepine (such as diazepam) may be administered intravenously. The clinician should be familiar, prior to use of local anesthetics, with these anticonvulsant drugs. Supportive treatment of circulatory depression may require administration of intravenous fluids and, when appropriate, a vasopressor as directed by the clinical situation (e.g., ephedrine).

If not treated immediately, both convulsions and cardiovascular depression can result in hypoxia, acidosis, bradycardia, arrhythmias and cardiac arrest. If cardiac arrest should occur, standard cardiopulmonary resuscitative measures should be instituted.

Endotracheal intubation, employing drugs and techniques familiar to the clinician, may be indicated, after initial administration of oxygen by mask, if difficulty is encountered in the maintenance of a patent airway or if prolonged ventilatory support (assisted or controlled) is indicated.

Dialysis is of negligible value in the treatment of acute overdosage with lidocaine.

The intravenous LD50 of Lidocaine HCl in female mice is 26 (21–31) mg/kg and the subcutaneous LD50 is 264 (203–304) mg/kg.

DOSAGE AND ADMINISTRATION

When 4% Lidocaine Hydrochloride Injection, USP is used concomitantly with other products containing lidocaine, the total dose contributed by all formulations must be kept in mind.

The dosage varies and depends upon the area to be anesthetized, vascularity of the tissues, individual tolerance and the technique of anesthesia. The lowest dosage needed to provide effective anesthesia should be administered. Dosages should be reduced for children and for elderly and debilitated patients.

Although the incidence of adverse effects with 4% Lidocaine Hydrochloride Injection, USP is quite low, caution should be exercised, particularly when employing large volumes and concentrations of lidocaine since the incidence of adverse effects is directly proportional to the total dose of local anesthetic agent administered.

For specific techniques and procedures refer to standard textbooks.

There have been adverse event reports of chondrolysis in patients receiving intra-articular infusions of local anesthetics following arthroscopic and other surgical procedures. 4% Lidocaine Hydrochloride Injection, USP is not approved for this use (see WARNINGS and DOSAGE AND ADMINISTRATION).

The dosages below are for normal, healthy adults.

RETROBULBAR INJECTION: The suggested dose for a 70 kg person is 3−5 mL (120−200 mg of lidocaine HCl), i.e., 1.7−3 mg/kg or 0.9−1.5 mg/lb body weight. A portion of this is injected retrobulbarly and the rest may be used to block the facial nerve.

TRANSTRACHEAL INJECTION: For local anesthesia by the transtracheal route 2−3 mL should be injected through a large enough needle so that the injection can be made rapidly. By injecting during inspiration some of the drug will be carried into the bronchi and the resulting cough will distribute the rest of the drug over the vocal cords and the epiglottis.

Occasionally it may be necessary to spray the pharynx by oropharyngeal spray to achieve complete analgesia. For the combination of the injection and spray, it should rarely be necessary to utilize more than 5 mL (200 mg of lidocaine HCl), i.e., 3 mg/kg or 1.5 mg/lb body weight.

TOPICAL APPLICATION: For laryngoscopy, bronchoscopy and endotracheal intubation, the pharynx may be sprayed with 1−5 mL (40−200 mg of lidocaine HCl), i.e., 0.6−3 mg/kg or 0.3−1.5 mg/lb body weight.

Maximum Recommended Dosages

Normal Healthy Adults: The maximum recommended dose of 4% Lidocaine Hydrochloride Injection, USP should be such that the dose of lidocaine HCl is kept below 300 mg and in any case should not exceed 4.5 mg/kg (2 mg/lb) body weight.

Children: It is difficult to recommend a maximum dose of any drug for children since this varies as a function of age and weight. For children of less than ten years who have a normal lean body mass and normal body development, the maximum dose may be determined by the application of one of the standard pediatric drug formulas (e.g., Clark's rule). For example, in a child of five years weighing 50 lbs, the dose of lidocaine hydrochloride should not exceed 75−100 mg when calculated according to Clark's rule. In any case, the maximum dose of lidocaine hydrochloride and epinephrine injection should not exceed 7 mg/kg (3.2 mg/lb) of body weight. When used without epinephrine, the amount of lidocaine administered should be such that the dose is kept below 300 mg and in any case should not exceed 4.5 mg/kg (2 mg/lb) of body weight.

NOTE: Parenteral drug products should be inspected visually for particulate matter and discoloration prior to administration whenever the solution and container permit. Solutions that are discolored and/or contain particulate matter should not be used. Do not use unless solution is clear and container undamaged.

HOW SUPPLIED

4% Lidocaine Hydrochloride Injection, USP is supplied in the following:

Unit of Sale | Concentration
NDC 0409-4283-01 Bundle of 5 Clamcells containing 5 Single-dose Ampuls per Clamcell | 4% 200 mg/5 mL (40 mg/mL)

Discard unused portion.

Store at 20 to 25°C (68 to 77°F). [See USP Controlled Room Temperature.]

Distributed by Hospira, Inc., Lake Forest, IL 60045 USA

LAB-1210-4.0

Revised: 7/2021

PRINCIPAL DISPLAY PANEL - 5 mL Ampule Label

5 mL Single-dose
Preservative-Free

NDC 0409-4283-11
Rx only

4%
Lidocaine HCl
Injection, USP

200 mg/5 mL (40 mg/mL)

ONLY FOR TOPICAL USE AND
RETROBULBAR INJECTION.

Dist. by Hospira, Inc., Lake Forest, IL 60045 USA

RL–7732

LOT ##–###–AA

EXP DMMMYYYY

PRINCIPAL DISPLAY PANEL - 5 mL Ampule Cello Pack Label

5 mL
5 Single-dose Ampuls
Rx only

Preservative-Free

NDC 0409-4283-25
Contains 5 of NDC 0409-4283-11

4%
Lidocaine HCl
Injection, USP
200 mg/5 mL
(40 mg/mL)

ONLY FOR TOPICAL USE AND RETROBULBAR INJECTION.

Each mL contains lidocaine hydrochloride, anhydrous 40 mg. May
contain HCl and/or NaOH for pH adjustment. pH 6.5 (5.0 to 7.0).
Usual dosage: See insert. Store at 20 to 25°C (68 to 77°F).
[See USP Controlled Room Temperature.]

Hospira

MADE IN SPAIN
Distributed by Hospira, Inc.,
Lake Forest, IL 60045 USA